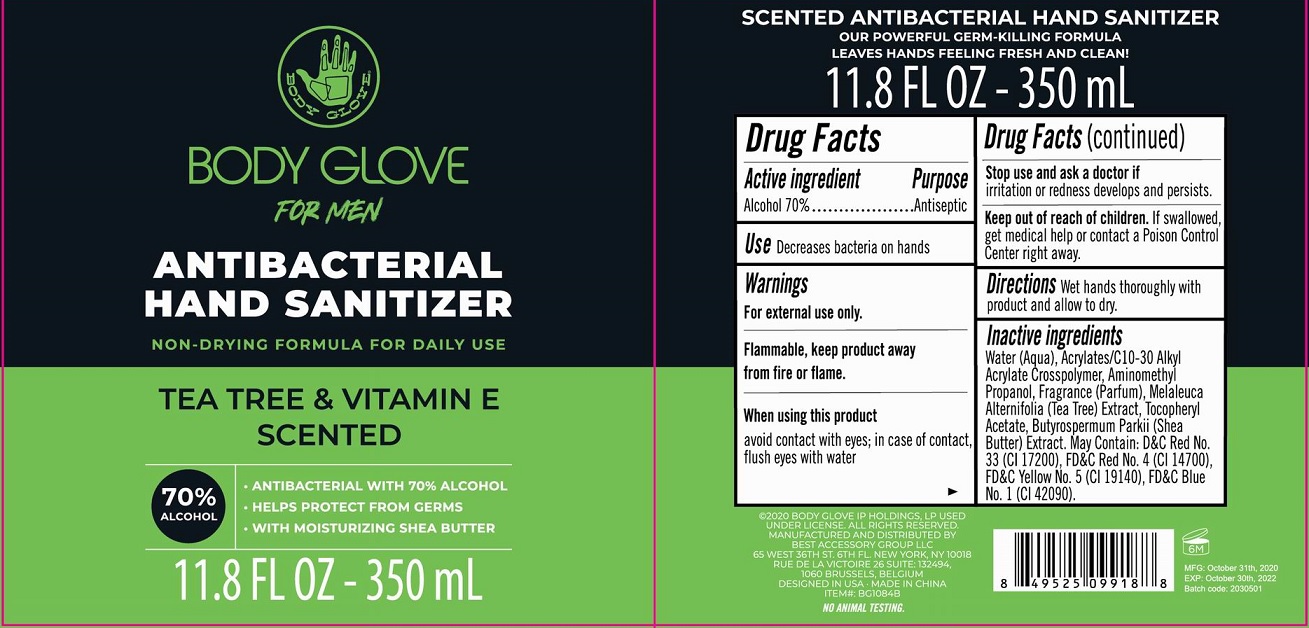 DRUG LABEL: Body Glove For Men Antibacterial Hand Sanitizer Tea Tree and Vitamin E Scented
NDC: 56136-497 | Form: LIQUID
Manufacturer: Ganzhou Olivee Cosmetic Co., Ltd.
Category: otc | Type: HUMAN OTC DRUG LABEL
Date: 20201113

ACTIVE INGREDIENTS: ALCOHOL 70 mL/100 mL
INACTIVE INGREDIENTS: WATER; CARBOMER COPOLYMER TYPE A; AMINOMETHYL PROPANEDIOL; .ALPHA.-TOCOPHEROL ACETATE, D-; SHEA BUTTER; FD&C RED NO. 3; FD&C RED NO. 4; FD&C YELLOW NO. 5; FD&C BLUE NO. 1; D&C RED NO. 33

Hand Wash

Active ingredient

Alcohol 70%

Purpose

Antibacterial

Use

Decreases bacteria on hands

Warnings

For external use only.

Flammbale, Keep product away from fire or flame.

When using this product

avoid contact with eyes; in case of contact, flush eyes with water.

Stop use and ask a doctor if

- irritation and redness develops and persists.

Keep out of reach of children.

If swallowed, get medical help or contact a Poison Control Center right away.

Directions

Wet hands thoroughly with product and allow to dry.

Inactive ingredients

Water (Aqua), Acrylates/C10-30 Alkyl Acrylate Crosspolymer, Aminomethyl Propanol, Fragrance (Parfum), Tocopheryl Acetate, Butyrospermum Parkii (Shea Butter) Extract. May contain: FD&C Red No. 4 (C.I. 14700), FD&C Yellow No. 5 (C.I. 19140), D&C Red No. 33 (Cl 17200), FD&C Blue No. 1 (Cl 42090).